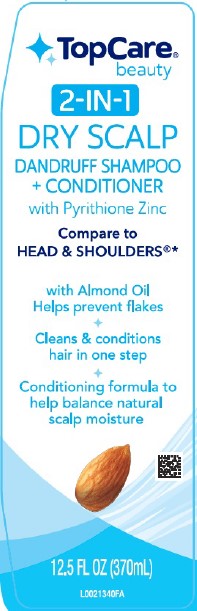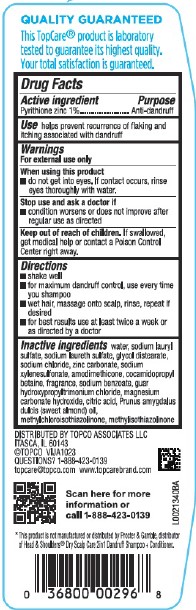 DRUG LABEL: Dry Scalp Care
NDC: 36800-497 | Form: SHAMPOO
Manufacturer: Topco Associates LLC
Category: otc | Type: HUMAN OTC DRUG LABEL
Date: 20260213

ACTIVE INGREDIENTS: PYRITHIONE ZINC 10 mg/1 mL
INACTIVE INGREDIENTS: WATER; SODIUM LAURYL SULFATE; SODIUM LAURETH SULFATE; GLYCOL DISTEARATE; SODIUM CHLORIDE; ZINC CARBONATE; SODIUM XYLENESULFONATE; AMODIMETHICONE (800 CST); COCAMIDOPROPYL BETAINE; SODIUM BENZOATE; GUAR HYDROXYPROPYLTRIMONIUM CHLORIDE (1.7 SUBSTITUENTS PER SACCHARIDE); MAGNESIUM CARBONATE HYDROXIDE; CITRIC ACID MONOHYDRATE; ALMOND OIL; METHYLCHLOROISOTHIAZOLINONE; METHYLISOTHIAZOLINONE

Top Care 296.007/296AT-AW
Dandruff Shampoo, Dry Scalp 2 in 1

Claims

QUALITY GUARANTEED

This TopCare®product is laboratory tested to guarantee its highest quality.

Your total satisfaction is quaranteed.

Active ingredient

Pyrithione zinc 1%

Purpose

Anti-dandruff

Use

helps prevent recurrence of flaking and itching associated with dandruff

Warnings

For external use only

When using this product

- do not get into eyes. If contact occurs, rinse eyes thoroughly with water.

Stop use and ask a doctor if

- condition worsens or does not improve after regular use as directed

Keep out of reach of children

If swallowed, get medical help or contact a Poison Control Center right away.

Directions

- shake well
- for maximum dandruff control, use every time you shampoo
- wet hair, massage onto scalp, rinse, repeat if desired
- for best results use at least twice a week or as directed by a doctor

Inactive ingredients

water, sodium lauryl sulfate, sodium laureth sulfate, glycol distearate, sodium chloride, zinc carbonate, sodium xylenesulfonate, amodimethicone, cocamidopropyl betaine, fragrance, sodium benzoate, guar hydroxypropyltrimonium chloride, magnesium carbonate hydroxide, citric acid, Prunus amygdalus dulcis (sweet almond) oil, methylchloroisothiazolinone, methylisothiazolinone

Adverse reactions

DISTRIBUTED BY TOPCO ASSOCIATES LLC

ITASCA, IL. 60143

©TOPCO VIJA1023

QUESTIONS? 1-888-423-0139

topcare@topco.com www.topcarebrand.com

Scan here for more information or call 1-888-423-0139

Disclaimer

*This product is not manufactured or distributed by Procter & Gamble, distributor of Heard & Shoulders®Dry Scalp Care 2in1 Dandruff Shampoo + Conditioner.

Principal display panel

TopCare®beauty

2-IN-1

DRY SCALP

DANDRUFF SHAMPOO + CONDITIONER

with Pyrithione Zinc

Compare to HEAD & SHOULDERS®*

with Almond Oil

Helps prevent flakes

Cleans & conditions hair in one step

Conditioning formula to help balance natural scalp moisture

12.5 FL OZ (370 mL)